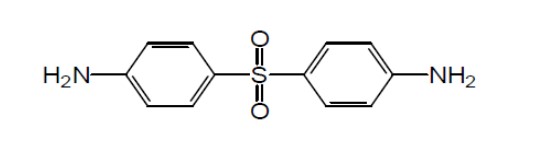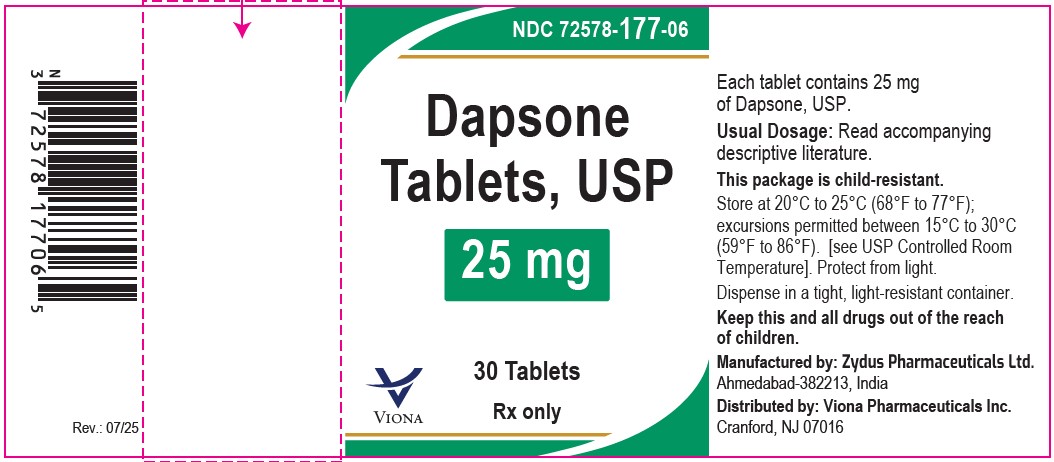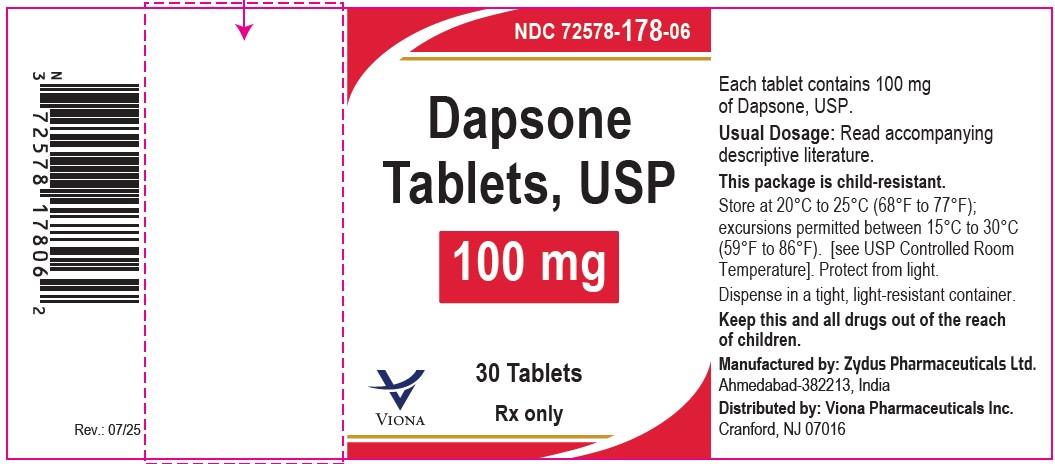 DRUG LABEL: Dapsone
NDC: 72578-177 | Form: TABLET
Manufacturer: Viona Pharmaceuticals Inc
Category: prescription | Type: HUMAN PRESCRIPTION DRUG LABEL
Date: 20260227

ACTIVE INGREDIENTS: DAPSONE 25 mg/1 1
INACTIVE INGREDIENTS: MICROCRYSTALLINE CELLULOSE; CROSCARMELLOSE SODIUM; HYDROXYPROPYL CELLULOSE, UNSPECIFIED; SILICON DIOXIDE; MAGNESIUM STEARATE

Dapsone Tablets, USP

DESCRIPTION

Dapsone USP, 4,4'-diaminodiphenylsulfone (DDS), is a primary treatment for Dermatitis herpetiformis. It is an antibacterial drug for susceptible cases of leprosy. It is a white or creamy white crystalline powder, insoluble in water, sparingly soluble in alcohol, freely soluble in acetone and in dilute mineral acids.

Dapsone is issued on prescription in tablets of 25 mg and 100 mg for oral use.

Each dapsone tablet, USP contains 25 mg and 100 mg of dapsone and contains following inactive ingredients: colloidal silicon dioxide, croscarmellose sodium, hydroxypropyl cellulose, magnesium stearate and microcrystalline cellulose.

FDA approved dissolution test specifications differ from USP.

CLINICAL PHARMACOLOGY

Actions: The mechanism of action in Dermatitis herpetiformis has not been established. By the kinetic method in mice, Dapsone is bactericidal as well as bacteriostatic against Mycobacterium leprae.

Absorption and Excretion: Dapsone, when given orally, is rapidly and almost completely absorbed. About 85 percent of the daily intake is recoverable from the urine mainly in the form of water-soluble metabolites. Excretion of the drug is slow and a constant blood level can be maintained with the usual dosage.

Blood Levels: Detected a few minutes after ingestion, the drug reaches peak concentration in 4 hours to 8 hours. Daily administration for at least eight days is necessary to achieve a plateau level. With doses of 200 mg daily, this level averaged 2.3 mcg/ml with a range of 0.1 mcg/ml to 7 mcg/ml. The half-life in the plasma in different individuals varies from ten hours to fifty hours and averages twenty-eight hours. Repeat tests in the same individual are constant. Daily administration (50 mg to 100 mg) in leprosy patients will provide blood levels in excess of the usual minimum inhibitory concentration even for patients with a short Dapsone half-life.

INDICATIONS AND USAGE

Dermatitis herpetiformis: (D.H.)

Leprosy: All forms of leprosy except for cases of proven Dapsone resistance.

CONTRAINDICATION

Hypersensitivity to Dapsone and/or its derivatives.

WARNINGS

The patient should be warned to respond to the presence of clinical signs such as sore throat, fever, pallor, purpura or jaundice. Deaths associated with the administration of Dapsone have been reported from agranulocytosis, aplastic anemia and other blood dyscrasias. Complete blood counts should be done frequently in patients receiving Dapsone. The FDA Dermatology Advisory Committee recommended that, when feasible, counts should be done weekly for the first month, monthly for six months and semi-annually thereafter. If a significant reduction in leucocytes, platelets or hemopoiesis is noted, Dapsone should be discontinued and the patient followed intensively. Folic acid antagonists have similar effects and may increase the incidence of hematologic reactions; if co-administered with Dapsone the patient should be monitored more frequently. Patients on weekly pyrimethamine and Dapsone have developed agranulocytosis during the second and third month of therapy.

Severe anemia should be treated prior to initiation of therapy and hemoglobin monitored. Hemolysis and methemoglobin may be poorly tolerated by patients with severe cardiopulmonary disease.

Cutaneous reactions, especially bullous, include exfoliative dermatitis and are probably one of the most serious, though rare, complications of sulfone therapy. They are directly due to drug sensitization. Such reactions include toxic erythema, erythema multiforme, toxic epidermal necrolysis, morbilliform and scarlatiniform reactions, urticaria and erythema nodosum. If new or toxic dermatologic reactions occur, sulfone therapy must be promptly discontinued and appropriate therapy instituted. Leprosy reactional states, including cutaneous, are not hypersensitivity reactions to Dapsone and do not require discontinuation. See special section.

PRECAUTIONS

General

Hemolysis and Heinz body formation may be exaggerated in individuals with a glucose-6-phosphate dehydrogenase (G6PD) deficiency, or methemoglobin reductase deficiency, or hemoglobin M. This reaction is frequently dose-related. Dapsone should be given with caution to these patients or if the patient is exposed to other agents or conditions such as infection or diabetic ketosis capable of producing hemolysis. Drugs or chemicals which have produced significant hemolysis in G6PD or methemoglobin reductase deficient patients include Dapsone, sulfanil amide, nitrite, aniline, phenylhydrazine, napthalene, niridazole, nitro-furantoin and 8-amino-antimalarials such as primaquine.

Toxic hepatitis and cholestatic jaundice have been reported early in therapy. Hyperbilirubinemia may occur more often in G6PD deficient patients. When feasible, baseline and subsequent monitoring of liver function is recommended; if abnormal, Dapsone should be discontinued until the source of the abnormality is established.

Falsely Reduced HbA1c

Falsely reduced HbA1c measurements have been reported with dapsone use. Alternate measures of glycemic control (e.g., fructosamine and/or more frequent blood glucose monitoring) are recommended when a discordance between HbA1c and blood glucose concentrations are observed or suspected. Falsely reduced HbA1c may occur without overt evidence of hemolysis or anemia.

Drug Interactions

Rifampin lowers Dapsone levels 7 to 10-fold by accelerating plasma clearance; in leprosy this reduction has not required a change in dosage. Folic acid antagonists such as pyrimethamine may increase the likelihood of hematologic reactions.

A modest interaction has been reported for patients receiving 100 mg Dapsone daily in combination with trimethoprim 5 mg/kg q6h. On Day 7, the serum Dapsone levels averaged 2.1 mcg/mL ± 1 mcg/mL in comparison to 1.5 mcg/mL ± 0.5 mcg/mL for Dapsone alone. On Day 7, trimethoprim levels averaged 18.4 mcg/mL ± 5.2 mcg/mL in comparison to 12.4 mcg/mL ± 4.5 mcg/mL for patients not receiving Dapsone. Thus, there is a mutual interaction between Dapsone and trimethoprim in which each raises the level of the other about 1.5 times.

A crossover study1 designed to assess the potential of a drug interaction between Dapsone, 100 mg/day and trimethoprim, 200 mg every 12 hours, in eight asymptomatic HIV positive volunteers (average CD4 count 524 cells/mm^3) demonstrated that there was not a significant drug intreraction between Dapsone and trimethoprim. However, an earlier report 2 also by Lee et al, in 78 HIV infected patients with acute Pneumocystis carinii pneumonia, receiving Dapsone, 100 mg/day and higher trimethoprim dose, 20 mg/kg/day, demonstrated that the serum levels of Dapsone were increased by 40% and trimethoprim levels were increased by 48% when the drugs were administered concurrently.

Carcinogenesis, mutagenesis

Dapsone has been found carcinogenic (sarcomagenic) for male rats and female mice causing mesenchymal tumors in the spleen and peritoneum and thyroid carcinoma in female rats. Dapsone is not mutagenic with or without microsomal activation in S. typhimurium tester strains 1535, 1537, 1538, 98 or 100.

Pregnancy

Teratogenic Effects. Animal reproduction studies have not been conducted with Dapsone. Extensive, but uncontrolled experience and two published surveys on the use of Dapsone in pregnant women have not shown that Dapsone increases the risk of fetal abnormalities if administered during all trimesters of pregnancy or can affect reproduction capacity. Because of the lack of animal studies or controlled human experience, Dapsone should be given to a pregnant woman only if clearly needed. In general, for leprosy, USPHS at Carville recommends maintenance of Dapsone. Dapsone has been important for the management of some pregnant D.H. patients.

Nursing Mothers

Dapsone is excreted in breast milk in substantial amounts. Hemolytic reactions can occur in neonates. See section on hemolysis. Because of the potential for tumorgenicity shown for Dapsone in animal studies a decision should be made whether to discontinue nursing or discontinue the drug taking into account the importance of drug to the mother.

Pediatric Use

Pediatric patients are treated on the same schedule as adults but with correspondingly smaller doses. Dapsone is generally not considered to have an effect on the later growth, development and functional development of the pediatric patient.

ADVERSE REACTIONS

In addition to the warnings listed above, the following syndromes and serious reactions have been reported in patients on Dapsone.

Hematologic Effects: Dose-related hemolysis is the most common adverse effect and is seen in patients with or without G6PD deficiency. Almost all patients demonstrate the inter-related changes of a loss of 1g to 2g of hemoglobin, an increase in the reticulocytes (2% to 12%), a shortened red cell life span and a rise in methemoglobin. G6PD deficient patients have greater responses.

Nervous System Effects: Peripheral neuropathy is a definite but unusual complication of Dapsone therapy in non-leprosy patients. Motor loss is predominant. If muscle weakness appears, Dapsone should be withdrawn. Recovery on withdrawal is usually substantially complete. The mechanism of recovery is reported by axonal regeneration. Some recovered patients have tolerated retreatment at reduced dosage. In leprosy this complication may be difficult to distinguish from a leprosy reactional state.

Falsely Reduced HbA1c: Falsely reduced HbA1c measurements have been reported with dapsone use. Alternate measures of glycemic control (e.g., fructosamine and/or more frequent blood glucose monitoring) are recommended when a discordance between HbA1c and blood glucose concentrations are observed or suspected. Falsely reduced HbA1c may occur without overt evidence of hemolysis or anemia.

Body As A Whole: In addition to the warnings and adverse effects reported above, additional adverse reactions include: nausea, vomiting, abdominal pains, pancreatitis, vertigo, blurred vision, tinnitus, insomnia, fever, headache, psychosis, phototoxicity, pulmonary eosinophilia, tachycardia, albuminuria, the nephrotic syndrome, hypoalbuminemia without proteinuria, renal papillary necrosis, male infertility, drug-induced Lupus erythematosus and an infectious mononucleosis-like syndrome. In general, with the exception of the complications of severe anoxia from overdosage (retinal and optic nerve damage, etc.) these adverse reactions have regressed off drug.

To report SUSPECTED ADVERSE REACTIONS, contact Viona Pharmaceuticals

Inc., at 1-888-304-5011 or FDA at 1-800-FDA-1088 or www.fda.gov/medwatch.

OVERDOSAGE

Nausea, vomiting, hyperexcitability can appear a few minutes up to 24 hours after ingestion of an overdosage. Methemoglobin induced depression, convulsions or severe cyanosis requires prompt treatment. In normal and methemoglobin reductase deficient patients, methylene blue, 1 mg/kg to 2 mg/kg of body weight, given slowly intravenously, is the treatment of choice. The effect is complete in 30 minutes, but may have to be repeated if methemoglobin reaccumulates. For non-emergencies, if treatment is needed, methylene blue may be given orally in doses of 3 mg/kg to 5 mg/kg every 4 hours to 6 hours. Methylene blue reduction depends on G6PD and should not be given to fully expressed G6PD deficient patients.

DOSAGE AND ADMINISTRATION

Dermatitis herpetiformis: The dosage should be individually titrated starting in adults with 50 mg daily and correspondingly smaller doses in children. If full control is not achieved within the range of 50 mg to 300 mg daily, higher doses may be tried. Dosage should be reduced to a minimum maintenance level as soon as possible. In responsive patients there is a prompt reduction in pruritus followed by clearance of skin lesions. There is no effect on the gastrointestinal component of the disease.

Dapsone levels are influenced by acetylation rates. Patients with high acetylation rates, or who are receiving treatment affecting acetylation may require an adjustment in dosage.

A strict gluten free diet is an option for the patient to elect, permitting many to reduce or eliminate the need for Dapsone; the average time for dosage reduction is 8 months with a range of 4 months to 2 1/2 years and for dosage elimination 29 months with a range of 6 months to 9 years.

Leprosy: In order to reduce secondary Dapsone resistance, the WHO Expert Committee on Leprosy and the USPHS at Carville, LA, recommended that Dapsone should be commenced in combination with one or more anti-leprosy drugs. In the multidrug program Dapsone should be maintained at the full dosage of 100 mg daily without interruption (with corresponding smaller doses for children) and provided to all patients who have sensitive organisms with new or recrudescent disease or who have not yet completed a two year course of Dapsone monotherapy. For advice and other drugs, the USPHS at Carville, LA (1-800-642-2477) should be contacted. Before using other drugs consult appropriate product labeling.

In bacteriologically negative tuberculoid and indeterminate disease, the recommendation is the coadministration of Dapsone 100 mg daily with six months of Rifampin 600 mg daily. Under WHO, daily Rifampin may be replaced by 600 mg Rifampin monthly, if supervised. The Dapsone is continued until all signs of clinical activity are controlled - usually after an additional six months. Then Dapsone should be continued for an additional three years for tuberculoid and indeterminate patients and for five years for borderline tuberculoid patients.

In lepromatous and borderline lepromatous patients, the recommendation is the coadministration of Dapsone 100 mg daily with two years of Rifampin 600 mg daily. Under WHO daily Rifampin may be replaced by 600 mg Rifampin monthly, if supervised. One may elect the concurrent administration of a third anti-leprosy drug, usually either Clofazamine 50 mg to 100 mg daily or Ethionamide 250 mg to 500 mg daily. Dapsone 100 mg daily is continued 3 years to 10 years until all signs of clinical activity are controlled with skin scrapings and biopsies negative for one year. Dapsone should then be continued for an additional 10 years for borderline patients and for life for lepromatous patients.

Secondary Dapsone resistance should be suspected whenever a lepromatous or borderline lepromatous patient receiving Dapsone treatment relapses clinically and bacteriologically, solid staining bacilli being found in the smears taken from the new active lesions. If such cases show no response to regular and supervised Dapsone therapy within three to six months or good compliance for the past 3 months to 6 months can be assured, Dapsone resistance should be considered confirmed clinically. Determination of drug sensitivity using the mouse footpad method is recommended and, after prior arrangement, is available without charge from the USPHS, Carville, LA. Patients with proven Dapsone resistance should be treated with other drugs.

LEPROSY REACTIONAL STATES

Abrupt changes in clinical activity occur in leprosy with any effective treatment and are known as reactional states. The majority can be classified into two groups.

The "Reversal" reaction (Type 1) may occur in borderline or tuberculoid leprosy patients often soon after chemotherapy is started. The mechanism is presumed to result from a reduction in the antigenic load: the patient is able to mount an enhanced delayed hypersensitivity response to residual infection leading to swelling ("Reversal") of existing skin and nerve lesions. If severe, or if neuritis is present, large doses of steroids should always be used. If severe, the patient should be hospitalized. In general anti-leprosy treatment is continued and therapy to suppress the reaction is indicated such as analgesics, steroids, or surgical decompression of swollen nerve trunks. USPHS at Carville, LA should be contacted for advice in management.

Erythema nodosum leprosum (ENL) (lepromatous reaction) (Type 2 reaction) occurs mainly in lepromatous patients and small numbers of borderline patients. Approximately 50% of treated patients show this reaction in the first year. The principal clinical features are fever and tender erythematous skin nodules sometimes associated with malaise, neuritis, orchitis, albuminuria, joint swelling, iritis, epistaxis or depression. Skin lesions can become pustular and/or ulcerate. Histologically there is a vasculitis with an intense polymorphonuclear infiltrate. Elevated circulating immune complexes are considered to be the mechanism of reaction. If severe, patients should be hospitalized. In general, anti-leprosy treatment is continued. Analgesics, steroids, and other agents available from USPHS, Carville, LA, are used to suppress the reaction.

HOW SUPPLIED

Dapsone Tablets USP, 25 mg are available as white to off white, round shaped tablets, scored on one side and debossed with '1713' on other side and are supplied as follows:

NDC 72578-177-06 in bottle of 30 tablets with child-resistant closure

NDC 72578-177-01 in bottle of 100 tablets with child-resistant closure

Dapsone Tablets USP, 100 mg are available as white to off white, round shaped tablets, scored on one side and debossed with '1714' on other side and are supplied as follows:

NDC 72578-178-06 in bottle of 30 tablets with child-resistant closure

NDC 72578-178-01 in bottle of 100 tablets with child-resistant closure

REFERENCES

1. Lee, B., et al., Zidovudine, Trimethoprim, and Dapsone Pharmacokinetic Interactions in Patients with HIV Infection. Antimicrobial Agents and Chemotherapy, May 1996; 1231-1236.

2. Lee, B., et al., Dapsone, Trimethoprim, and Sulfamethoxazole Plasma Levels During Treatment of Pneumocystis Carinii Pneumonia in Patients with AIDS, Annals of Internal Medicine, 1989; 110:606-611.

Store at 20°C to 25°C (68°F to 77°F); excursions permitted between 15°C to 30°C (59°F to 86°F). [see USP Controlled Room Temperature].

Protect from light.

Rx only. Keep this and all drugs out of the reach of children.

Manufactured by:

Zydus Pharmaceuticals Ltd.

Ahmedabad-382213, India

Distributed by:

Viona Pharmaceuticals Inc.

Cranford, NJ 07016

Rev.:07/25

PACKAGE LABEL.PRINCIPAL DISPLAY PANEL

NDC 72578-177-06 in bottle of 30 tablets

Dapsone Tablets USP, 25 mg

Rx only

30 tablets

NDC 72578-178-06 in bottle of 30 tablets

Dapsone Tablets USP, 100 mg

Rx only

30 tablets